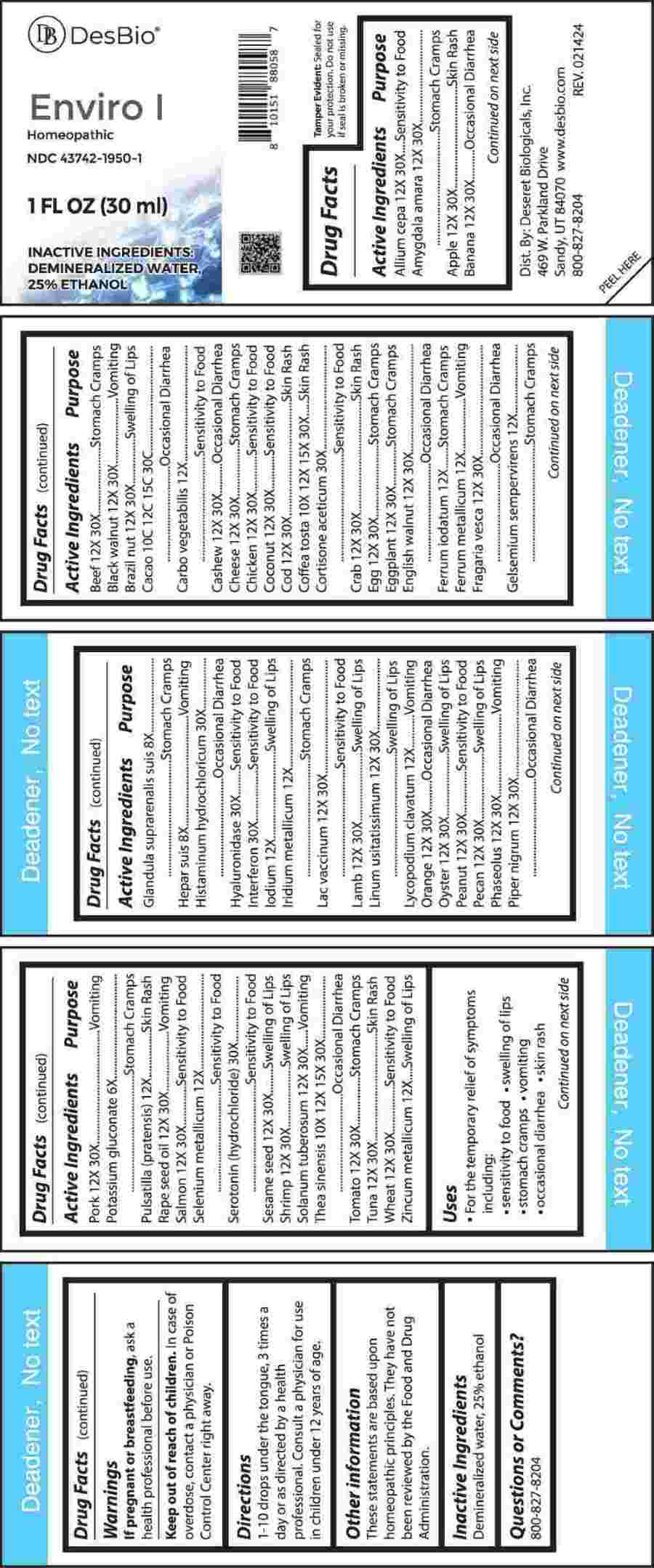 DRUG LABEL: Enviro I
NDC: 43742-1950 | Form: LIQUID
Manufacturer: Deseret Biologicals, Inc.
Category: homeopathic | Type: HUMAN OTC DRUG LABEL
Date: 20240417

ACTIVE INGREDIENTS: POTASSIUM GLUCONATE 6 [hp_X]/1 mL; SUS SCROFA ADRENAL GLAND 8 [hp_X]/1 mL; PORK LIVER 8 [hp_X]/1 mL; COFFEA ARABICA SEED, ROASTED 10 [hp_X]/1 mL; GREEN TEA LEAF 10 [hp_X]/1 mL; ACTIVATED CHARCOAL 12 [hp_X]/1 mL; FERROUS IODIDE 12 [hp_X]/1 mL; IRON 12 [hp_X]/1 mL; GELSEMIUM SEMPERVIRENS ROOT 12 [hp_X]/1 mL; IODINE 12 [hp_X]/1 mL; IRIDIUM 12 [hp_X]/1 mL; LYCOPODIUM CLAVATUM SPORE 12 [hp_X]/1 mL; PULSATILLA PRATENSIS WHOLE 12 [hp_X]/1 mL; SELENIUM 12 [hp_X]/1 mL; ZINC 12 [hp_X]/1 mL; PEANUT 12 [hp_X]/1 mL; BLACK WALNUT 12 [hp_X]/1 mL; ENGLISH WALNUT 12 [hp_X]/1 mL; BITTER ALMOND 12 [hp_X]/1 mL; CASHEW 12 [hp_X]/1 mL; COCONUT 12 [hp_X]/1 mL; PECAN 12 [hp_X]/1 mL; BRAZIL NUT 12 [hp_X]/1 mL; TOMATO 12 [hp_X]/1 mL; SOLANUM TUBEROSUM WHOLE 12 [hp_X]/1 mL; GREEN PEPPERCORN 12 [hp_X]/1 mL; EGGPLANT 12 [hp_X]/1 mL; CANOLA OIL 12 [hp_X]/1 mL; FLAX SEED 12 [hp_X]/1 mL; SESAME SEED 12 [hp_X]/1 mL; CASEIN, LACTOCOCCUS LACTIS CULTURED, PENICILLIUM ROQUEFORTI CULTURED, AGED 12 [hp_X]/1 mL; COW MILK 12 [hp_X]/1 mL; BEEF 12 [hp_X]/1 mL; LAMB 12 [hp_X]/1 mL; PORK 12 [hp_X]/1 mL; CHICKEN 12 [hp_X]/1 mL; EGG 12 [hp_X]/1 mL; KIDNEY BEAN 12 [hp_X]/1 mL; ONION 12 [hp_X]/1 mL; APPLE 12 [hp_X]/1 mL; WHEAT 12 [hp_X]/1 mL; BANANA 12 [hp_X]/1 mL; FRAGARIA VESCA FRUIT 12 [hp_X]/1 mL; ORANGE 12 [hp_X]/1 mL; ATLANTIC COD 12 [hp_X]/1 mL; NORTHERN BLUEFIN TUNA 12 [hp_X]/1 mL; ATLANTIC SALMON 12 [hp_X]/1 mL; EDIBLE ROCK CRAB 12 [hp_X]/1 mL; PACIFIC OYSTER 12 [hp_X]/1 mL; COMMON SHRIMP 12 [hp_X]/1 mL; CORTISONE ACETATE 30 [hp_X]/1 mL; HISTAMINE DIHYDROCHLORIDE 30 [hp_X]/1 mL; HYALURONIDASE 30 [hp_X]/1 mL; INTERFERON .GAMMA. PORCINE RECOMBINANT 30 [hp_X]/1 mL; SEROTONIN HYDROCHLORIDE 30 [hp_X]/1 mL; COCOA 10 [hp_C]/1 mL
INACTIVE INGREDIENTS: WATER; ALCOHOL

DRUG FACTS:

ACTIVE INGREDIENTS:

Allium Cepa 12X, 30X, Amygdala Amara 12X, 30X, Apple 12X, 30X, Banana 12X, 30X, Beef 12X, 30X, Black Walnut 12X, 30X, Brazil Nut 12X, 30X, Cacao 10C, 12C, 15C, 30C, Carbo Vegetabilis 12X, Cashew 12X, 30X, Cheese 12X, 30X, Chicken 12X, 30X, Coconut 12X, 30X, Cod 12X, 30X, Coffea Tosta 10X, 12X, 15X, 30X, Cortisone Aceticum 30X, Crab 12X, 30X, Egg 12X, 30X, Eggplant 12X, 30X, English Walnut 12X, 30X, Ferrum Iodatum 12X, Ferrum Metallicum 12X, Fragaria Vesca 12X, 30X, Gelsemium Sempervirens 12X, Glandula Suprarenalis Suis 8X, Hepar Suis 8X, Histaminum Hydrochloricum 30X, Hyaluronidase 30X, Interferon 30X, Iodium 12X, Iridium Metallicum 12X, Lac Vaccinum 12X, 30X, Lamb 12X, 30X, Linum Usitatissimum 12X, 30X, Lycopodium Clavatum 12X, Orange 12X, 30X, Oyster 12X, 30X, Peanut 12X, 30X, Pecan 12X, 30X, Phaseolus 12X, 30X, Piper Nigrum 12X, 30X, Pork 12X, 30X, Potassium Gluconate 6X, Pulsatilla (Pratensis) 12X, Rape Seed Oil 12X, 30X, Salmon 12X, 30X, Selenium Metallicum 12X, Serotonin (Hydrochloride) 30X, Sesame Seed 12X, 30X, Shrimp 12X, 30X, Solanum Tuberosum 12X, 30X, Thea Sinensis 10X, 12X, 15X, 30X, Tomato 12X, 30X, Tuna 12X, 30X, Wheat 12X, 30X, Zincum Metallicum 12X.

PURPOSE:

Allium Cepa – Sensitivity to Food, Amygdala Amara – Stomach Cramps, Apple – Skin Rash, Banana – Occasional Diarrhea, Beef – Stomach Cramps, Black Walnut - Vomiting, Brazil Nut – Swelling of Lips, Cacao – Occasional Diarrhea, Carbo Vegetabilis – Sensitivity to Food, Cashew – Occasional Diarrhea, Cheese – Stomach Cramps, Chicken – Sensitivity to Food, Coconut – Sensitivity to Food, Cod – Skin Rash, Coffea Tosta – Skin Rash, Cortisone Aceticum – Sensitivity to Food, Crab – Skin Rash, Egg – Stomach Cramps, Eggplant – Stomach Cramps, English Walnut – Occasional Diarrhea, Ferrum Iodatum – Stomach Cramps, Ferrum Metallicum - Vomiting, Fragaria Vesca – Occasional Diarrhea, Gelsemium Sempervirens – Stomach Cramps, Glandula Suprarenalis Suis – Stomach Cramps, Hepar Suis - Vomiting, Histaminum Hydrochloricum – Occasional Diarrhea, Hyaluronidase – Sensitivity to Food, Interferon – Sensitivity to Food, Iodium – Swelling of Lips, Iridium Metallicum – Stomach Cramps, Lac Vaccinum – Sensitivity to Food, Lamb – Swelling of Lips, Linum Usitatissimum – Swelling of Lips, Lycopodium Clavatum - Vomiting, Orange – Occasional Diarrhea, Oyster – Swelling of Lips, Peanut – Sensitivity to Food, Pecan - Swelling of Lips, Phaseolus - Vomiting, Piper Nigrum – Occasional Diarrhea, Pork - Vomiting, Potassium Gluconate – Stomach Cramps, Pulsatilla (Pratensis) – Skin Rash, Rape Seed Oil - Vomiting, Salmon – Sensitivity to Food, Selenium Metallicum – Sensitivity to Food, Serotonin (Hydrochloride) – Sensitivity to Food, Sesame Seed – Swelling of Lips, Shrimp – Swelling of Lips, Solanum Tuberosum - Vomiting, Thea Sinensis – Occasional Diarrhea, Tomato – Stomach Cramps, Tuna – Skin Rash, Wheat – Sensitivity to Food, Zincum Metallicum – Swelling of Lips

USES:

• For the temporary relief of symptoms including:

• sensitivity to food • swelling of lips • stomach cramps

• vomiting • occasional diarrhea • skin rash

These statements are based upon homeopathic principles. They have not been reviewed by the Food and Drug Administration.

WARNINGS:

If pregnant or breast-feeding, ask a health professional before use.

Keep out of reach of children. In case of overdose, contact a physician or Poison Control Center right away.

Tamper Evident: Sealed for your protection. Do not use if seal is broken or missing.

KEEP OUT OF REACH OF CHILDREN:

In case of overdose, contact a physician or Poison Control Center right away.

DIRECTIONS:

1-10 drops under the tongue, 3 times a day or as directed by a health professional. Consult a physician for use in children under 12 years of age.

INACTIVE INGREDIENTS:

Demineralized water, 25% ethanol

QUESTIONS:

Dist. By: Deseret Biologicals, Inc.

469 W. Parkland Drive

Sandy, UT 84070

www.desbio.com

800-827-8204

PACKAGE LABEL DISPLAY:

Des Bio

Enviro I

Homeopathic
NDC 43742-1950-1
1 FL OZ (30 ml)